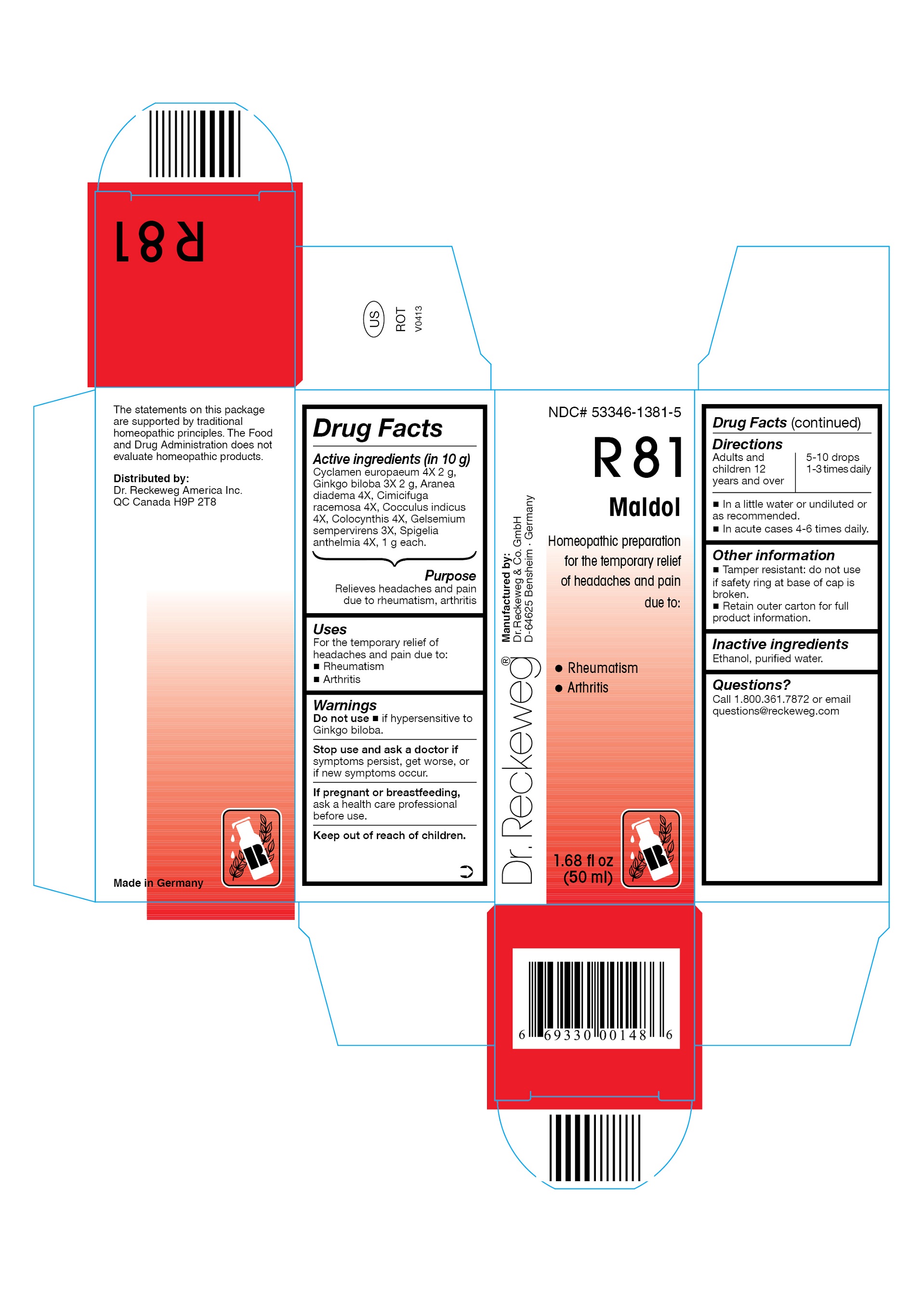 DRUG LABEL: DR. RECKEWEG R81 Maldol
NDC: 53346-1381 | Form: LIQUID
Manufacturer: PHARMAZEUTISCHE FABRIK DR. RECKEWEG & CO
Category: homeopathic | Type: HUMAN OTC DRUG LABEL
Date: 20130403

ACTIVE INGREDIENTS: CYCLAMEN PURPURASCENS TUBER 4 [hp_X]/50 mL; GINKGO 3 [hp_X]/50 mL; ARANEUS DIADEMATUS 4 [hp_X]/50 mL; BLACK COHOSH 4 [hp_X]/50 mL; ANAMIRTA COCCULUS SEED 4 [hp_X]/50 mL; CITRULLUS COLOCYNTHIS FRUIT PULP 4 [hp_X]/50 mL; GELSEMIUM SEMPERVIRENS ROOT 3 [hp_X]/50 mL; SPIGELIA ANTHELMIA 4 [hp_X]/50 mL
INACTIVE INGREDIENTS: ALCOHOL; WATER

DR. RECKEWEG R81 Maldol

Active ingredients

Cyclamen europaeum 4X 2 g, Ginkgo biloba 3X 2 g, Aranea diadema 4X, Cimicifuga racemosa 4X, Cocculus indicus 4X, Colocynthis 4X, Gelsemium sempervirens 3X, Spigelia anthelmia 4X, 1 g each in 10 g.

Purpose

Relieves headaches and pain due to rheumatism, arthritis

Uses
For the temporary relief of headaches and pain due to:

- Rheumatism
- Arthritis

Warnings

Do not use

- if hypersensitive to Ginkgo biloba.

Stop use and ask a doctor if symptoms persist, get worse, or if new symptoms occur.

PREGNANCY OR BREAST FEEDING

If pregnant or breastfeeding, ask a health care professional before use.

Keep out of reach of children.

Directions
Adults and children ≥ 12 years 5-10 drops 1-3 times daily, in acute cases 4-6

times daily in a little water or undiluted or as recommended.

Other information

- Tamper resistant: do not use if safety ring at base of cap is broken.
- Retain outer carton for full product information.

Inactive ingredients

Ethanol, purified water.

Questions?
Call 1-800-361-7872 or email questions@reckeweg.com

PACKAGE LABEL

NDC# 53346-1381-5

Dr. Reckeweg R81 Maldol

Homeopathic preparation for the temporary relief of headaches and pain due to:

- Rheumatism
- Arthritis

Manufactured by:

Dr. Reckeweg Co. GmbH

D-64625 Bensheim

Germany

1.68 fl oz
(50 ml)